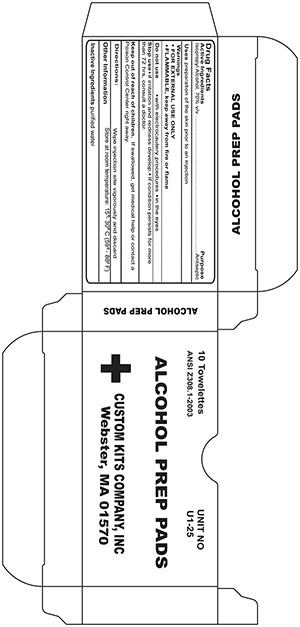 DRUG LABEL: Alcohol Prep
NDC: 68183-117 | Form: CLOTH
Manufacturer: Custom Kits Company Inc
Category: otc | Type: HUMAN OTC DRUG LABEL
Date: 20200117

ACTIVE INGREDIENTS: ISOPROPYL ALCOHOL 0.7 mL/0.7 mL
INACTIVE INGREDIENTS: WATER

Alcohol Prep Pads

Active Ingredient

Isopropyl Alcohol 70% v/v

Purpose

Antiseptic

Uses

- Antiseptic Cleanser
- Kills harmful bacteria and germs
- First Aid to Help Prevent Infection

Warnings

- For External Use Only
- Avoid contact with the eyes

If contact occurs, flush eyes with water

Flammable, keep away from flame or fire.

Do Not Use

With electrocautery, in the eyes

Stop use and ask a doctor if

Irritation and redness develops

If condition persists for more than 72 hours, consult a physician

Keep out of reach of children

If swallowed, get medical help or contact a Posion Control Center right away

Directions

Use as a part of your daily cleansing routine

May be covered with a sterile bandage

Other Safety Information

Store at room temperature 15-30 C (59-86 F)

Avoid Excess Heat

Inactive Ingredients

Water